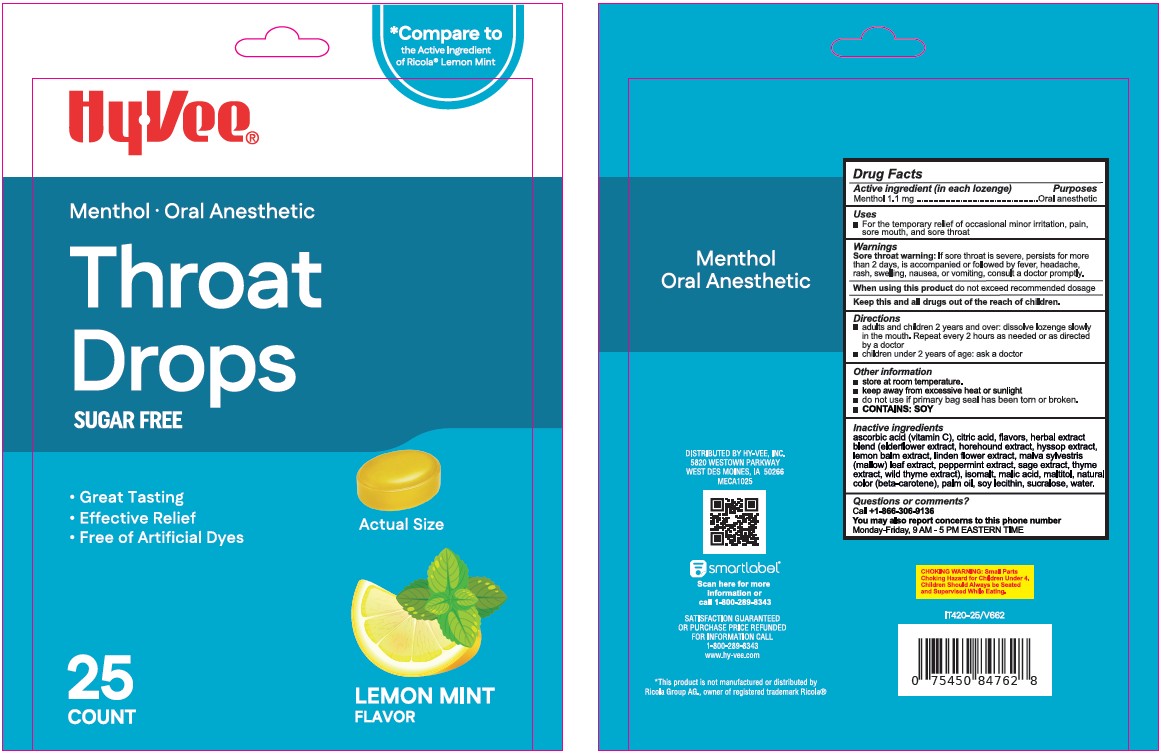 DRUG LABEL: HyVee Throat Drops Lemon Mint
NDC: 83698-907 | Form: LOZENGE
Manufacturer: Xiamen Kang Zhongyuan Biotechnology Co., Ltd.
Category: otc | Type: HUMAN OTC DRUG LABEL
Date: 20260108

ACTIVE INGREDIENTS: MENTHOL 1.1 mg/1 1
INACTIVE INGREDIENTS: ASCORBIC ACID; CITRIC ACID; ISOMALT; MALIC ACID; SAMBUCUS NIGRA FLOWER; HOREHOUND; HYSSOPUS OFFICINALIS FLOWERING TOP; LEMON BALM OIL; TILIA CORDATA FLOWER; MALVA SYLVESTRIS LEAF; PEPPERMINT; SAGE; THYME; WILD THYME; MALTITOL; BETA CAROTENE; PALM OIL; LECITHIN, SOYBEAN; SUCRALOSE

Lemon Mint Flavor Menthol Cough Drop HY-VEE - Xiamen

Drug Facts

Purpose

Oral anesthetic

Active Ingredient (in each drop)

Menthol 1.1 mg

Uses

- for the temporary relief of occasional minor irritation, pain, sore mouth, and sore throat

Warnings

Sore throat warning:If sore throat is severe, persists for more than 2 days, is accompanied or followed by fever, headache, rash, swelling, nausea, or vomiting, consult a doctor promptly.

When using this productdo not exceed recommended dosage

Directions

- Adults and children 2 years of age and older: Dissolve lozenge slowly in the mouth. May be repeated every 2 hours as needed or as directed by a dentist or doctor.
- Children under 2 years of age: ask a doctor.

Other Information

- store at room temperature.
- keep away from excessive heat or sunlight
- do not use if primary bag seal has been torn or broken.
- contains: SOY

Inactive Ingredients

ascorbic acid (vitamin C), citric acid, flavors,
Herbal extract blend (elderflower extract, horehound extract,
hyssop extract, lemon balm extract, linden flower extract, malva
sylvestris (mallow) leaf extract, peppermint extract, sage extract, thyme
extract, wild thyme extract), isomalt, malic acid, maltitol, natural color
(beta-carotene), palm oil, soy lecithin, sucralose, water.

Questions or comments?

Call +1-866-306-9136

You may also report concerns to this phone number

Monday to Friday, 9 AM - 5 PM Eastern Time